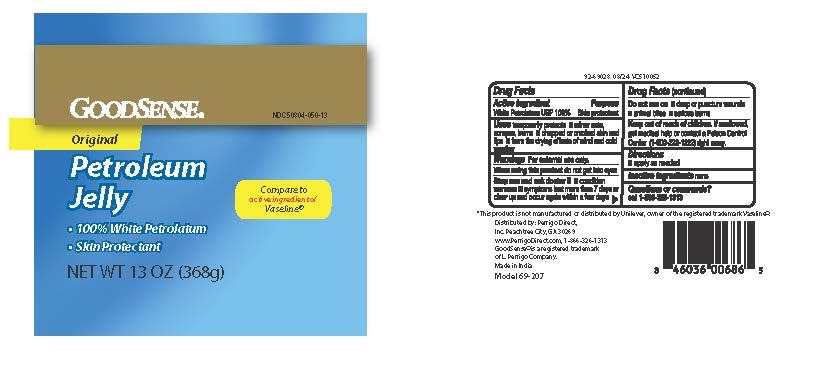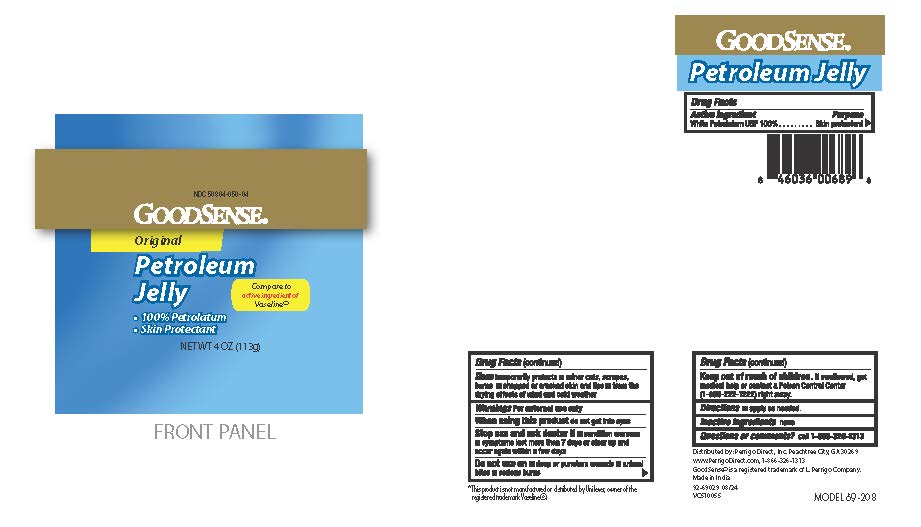 DRUG LABEL: GoodSense Petroleum Jelly
NDC: 50804-050 | Form: JELLY
Manufacturer: GOOD SENSE
Category: otc | Type: HUMAN OTC DRUG LABEL
Date: 20250929

ACTIVE INGREDIENTS: PETROLATUM 100 g/100 g
INACTIVE INGREDIENTS: WATER

GoodSense Petroleum Jelly

Drug Facts

ACTIVE INGREDIENT

White Petroleum USP 100%

Active ingredients | Purpose
White Petrolatum 100% | Skin Protectant

Uses

temporarily protects:

- minor cuts, scrapes, burns
- chapped or cracked skin and lips
- from the drying effects of wind and cold weather

Warnings

For external use only

When using this product

- do not get into eyes

Stop use and ask a doctor if

- condition worsens
- symptoms last more than 7 days or clear up and occur again within a few days

Do not use on

- deep or puncture wounds .
- animal bites
- serious burns.

Keep out of reach of children.If swallowed, get medical help or contact a Poison Control Center (1-800-222-1222) right away.

Directions

Apply as needed

Inactive ingredient

Water